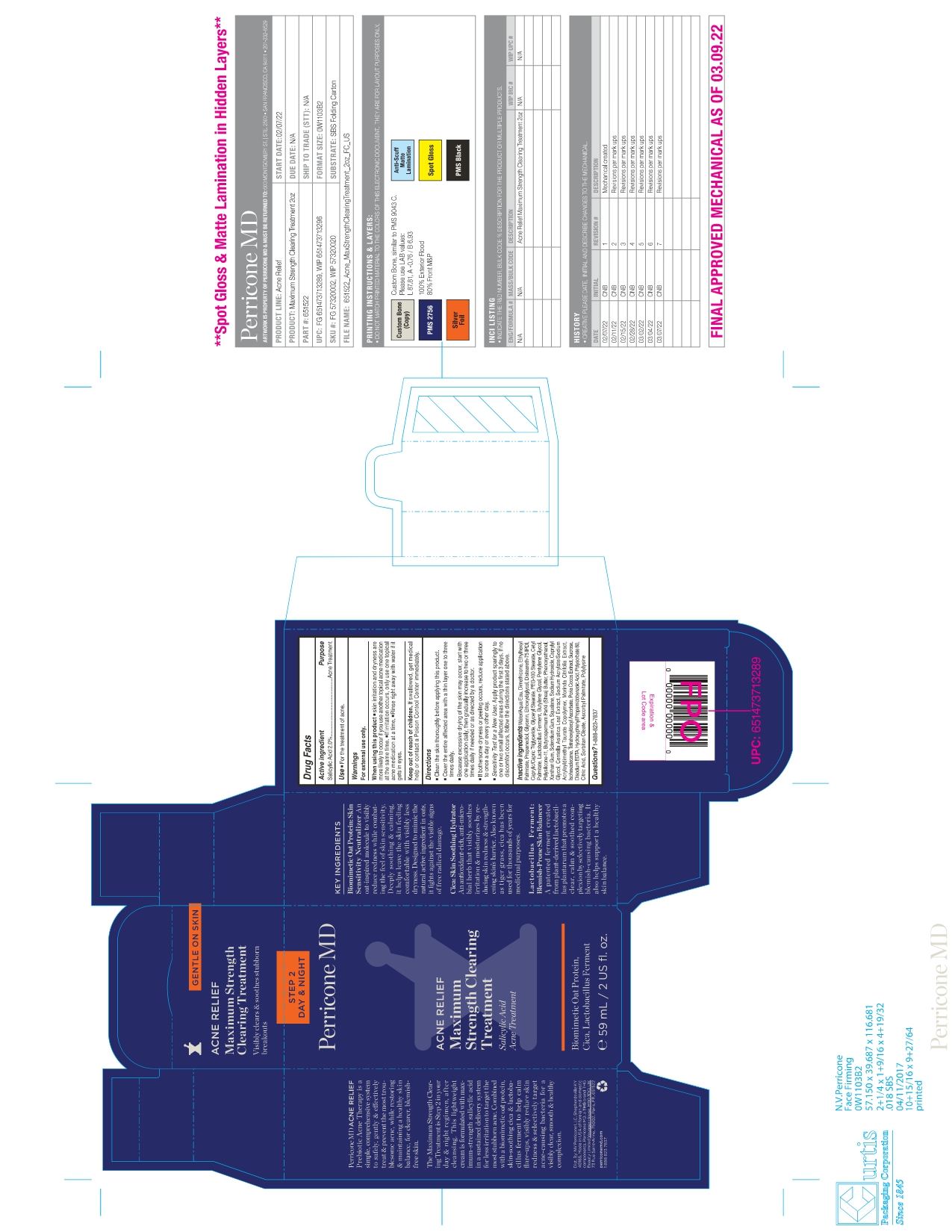 DRUG LABEL: Perricone MD Acne Relief Maximum Strength Clearing Treatment
NDC: 84448-301 | Form: CREAM
Manufacturer: THG Beauty USA LLC
Category: otc | Type: HUMAN OTC DRUG LABEL
Date: 20251107

ACTIVE INGREDIENTS: SALICYLIC ACID 2 g/100 mL
INACTIVE INGREDIENTS: PENTYLENE GLYCOL; SHEA BUTTER; PHENOXYETHANOL; CAPRYLYL GLYCOL; EDETATE DISODIUM; DISTEARETH-75 ISOPHORONE DIISOCYANATE; WATER; MEDIUM-CHAIN TRIGLYCERIDES; CENTELLA ASIATICA LEAF; TETRAHEXYLDECYL ASCORBATE; CITRIC ACID MONOHYDRATE; POLYSORBATE 80; BUTYLENE GLYCOL; BETASIZOFIRAN; ISOHEXADECANE; DIMETHICONE; DIMETHICONE/VINYL DIMETHICONE CROSSPOLYMER (SOFT PARTICLE); PROPANEDIOL; CETYL PALMITATE; ETHYLHEXYL PALMITATE; GLYCERYL MONOSTEARATE; PEG-100 STEARATE; LIMOSILACTOBACILLUS FERMENTUM; SQUALANE; GLYCERIN; SODIUM HYDROXIDE; XANTHAN GUM; SODIUM ACRYLATE/SODIUM ACRYLOYLDIMETHYLTAURATE COPOLYMER (4000000 MW); MORINDA CITRIFOLIA WHOLE; FU LING; SUCROSE; HYDROXYPHENYL PROPAMIDOBENZOIC ACID; SORBITAN MONOOLEATE; ASCORBYL PALMITATE; POLY-L-LYSINE (30000-70000 MW); ETHOXYDIGLYCOL

ACTIVE INGREDIENT

Salicylic Acid 2%

PURPOSE

Acne Treatment

INDICATIONS AND USAGE

For the treatment of acne.

WARNINGS

For external use only.

When using this product

■ skin irritation and dryness are more likely to occur if you use another topical acne medication at the same time.

■ If irritation occurs, only use one topical acne medication at a time.

■ Rinse right away with water if it gets in eyes.

Keep out of reach of children. If swallowed, get medical help or contact a Poison Control Centre immediately.

Directions

■ Clean the skin thoroughly before applying this product.

■ Cover the entire affected area with a thin layer one to three times daily.
■ Because excessive drying of the skin may occur, start with one application daily, then gradually increase to two or three times daily if needed or as directed by a doctor.
■ If bothersome dryness or peeling occurs, reduce application to once a day or every other day.
■ Sensitivity Test for a New User. Apply product sparingly to one or two small affected areas during the first 3 days. If no discomfort occurs, follow the directions stated above.

INACTIVE INGREDIENT

Water/Aqua/Eau, Dimethicone, Ethylhexyl Palmitate, Propanediol, Glycerin, Ethoxydiglycol, Disteareth-75 IPDI, Caprylic/Capric Triglyceride, Glyceryl Stearate, PEG-100 Stearate, Cetyl Palmitate, Lactobacillus Ferment, Butylene Glycol, Pentylene Glycol,
Polysilicone-11, Butyrospermum Parkii (Shea) Butter, Phenoxyethanol, Xanthan Gum, Sclerotium Gum, Squalane, Sodium Hydroxide, Caprylyl Glycol, Centella Asiatica Leaf Extract, Sodium Acrylate/Sodium Acryloyldimethyl Taurate Copolymer, Morinda Citrifolia Extract, Isohexadecane, Tetrahexyldecyl Ascorbate, Poria Cocos Extract, Sucrose, Disodium EDTA, Hydroxyphenyl Propamidobenzoic Acid, Polysorbate 80, Citric Acid, Sorbitan Oleate, Ascorbyl Palmitate, Polylysine

QUESTIONS

1-888-823-7837